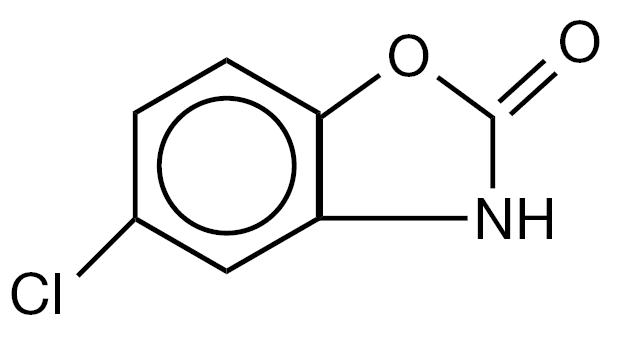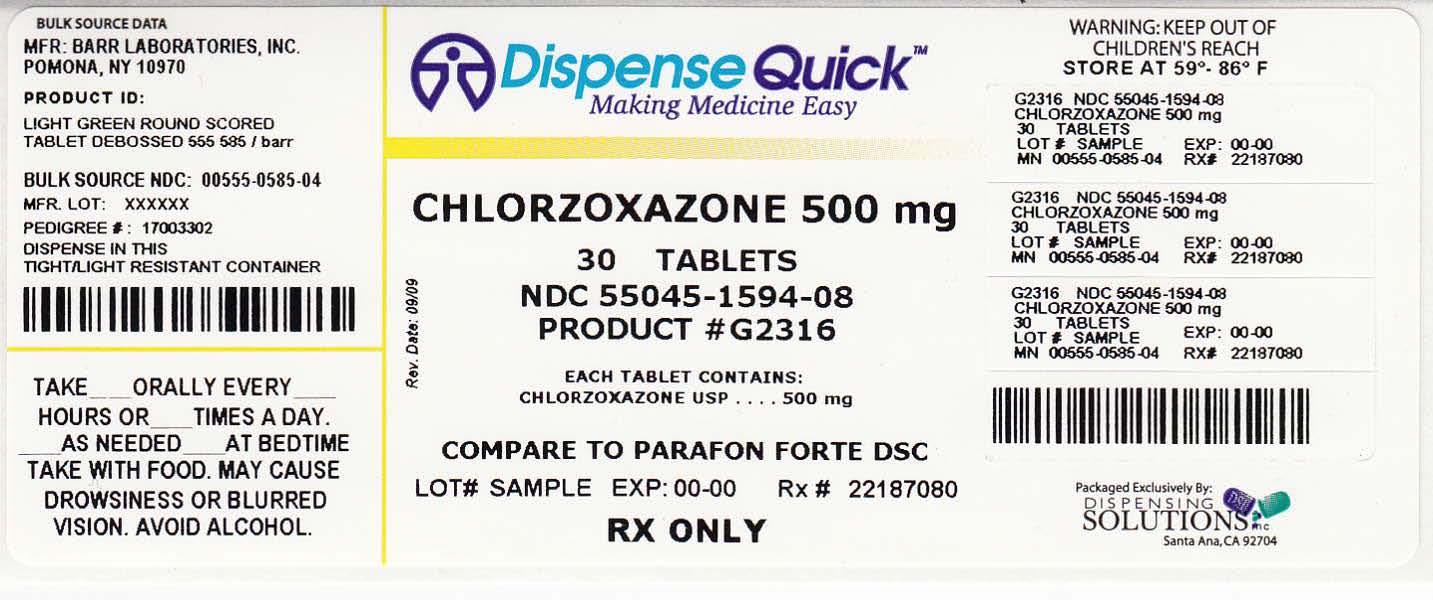 DRUG LABEL: Chlorzoxazone
NDC: 55045-1594 | Form: TABLET
Manufacturer: Dispensing Solutions, Inc.
Category: prescription | Type: HUMAN PRESCRIPTION DRUG LABEL
Date: 20110907

ACTIVE INGREDIENTS: CHLORZOXAZONE 500 mg/1 1
INACTIVE INGREDIENTS: SILICON DIOXIDE; CROSCARMELLOSE SODIUM; DOCUSATE SODIUM; MAGNESIUM STEARATE; CELLULOSE, MICROCRYSTALLINE; SODIUM BENZOATE; D&C YELLOW NO. 10; FD&C BLUE NO. 1; ALUMINUM OXIDE

CHLORZOXAZONE TABLETS, USP

Revised SEPTEMBER 2002

1005850104

Rx only

DESCRIPTION:

Each tablet contains:

Chlorzoxazone…………500 mg

Inactive Ingredients: Colloidal silicon dioxide, croscarmellose sodium, docusate sodium, lactose anhydrous, magnesium stearate, microcrystalline cellulose, sodium benzoate, D&C yellow no. 10 aluminum lake, FD&C blue no. 1 aluminum lake HT.

5-chloro-2-benzoxazolinone. The structural formula is as follows:

C7H4ClNO2 Molecular Weight:169.57

CLINICAL PHARMACOLOGY:

Chlorzoxazone is a centrally-acting agent for painful musculoskeletal conditions. Data available from animal experiments as well as human study indicate that chlorzoxazone acts primarily at the level of the spinal cord and subcortical areas of the brain where it inhibits multi-synaptic reflex arcs involved in producing and maintaining skeletal muscle spasm of varied etiology. The clinical result is a reduction of the skeletal muscle spasm with relief of pain and increased mobility of the involved muscles. Blood levels of chlorzoxazone can be detected in people during the first 30 minutes and peak levels may be reached, in the majority of the subjects, in about 1 to 2 hours after oral administration of chlorzoxazone. Chlorzoxazone is rapidly metabolized and is excreted in the urine, primarily in a conjugated form as the glucuronide. Less than one percent of a dose of chlorzoxazone is excreted unchanged in the urine in 24 hours.

INDICATIONS AND USAGE:

Chlorzoxazone tablets are indicated as an adjunct to rest, physical therapy, and other measures for the relief of discomfort associated with acute painful musculoskeletal conditions. The mode of action of this drug has not been clearly identified but may be related to its sedative properties. Chlorzoxazone does not directly relax tense skeletal muscles in man.

CONTRAINDICATIONS:

Chlorzoxazone tablets are contraindicated in patients with known intolerance to the drug.

WARNINGS:

Serious (including fatal) hepatocellular toxicity has been reported rarely in patients receiving chlorzoxazone. The mechanism is unknown but appears to be idiosyncratic and unpredictable. Factors predisposing patients to this rare event are not known. Patients should be instructed to report early signs and/or symptoms of hepatotoxicity such as fever, rash, anorexia, nausea, vomiting, fatigue, right upper quadrant pain, dark urine, or jaundice. Chlorzoxazone should be discontinued immediately and a physician consulted if any of these signs or symptoms develop. Chlorzoxazone use should also be discontinued if a patient develops abnormal liver enzymes (e.g., AST, ALT, alkaline phosphatase and bilirubin).

The concomitant use of alcohol or other central nervous system depressants may have an additive effect.

Usage in Pregnancy:

The safe use of chlorzoxazone has not been established with respect to the possible adverse effects upon fetal development. Therefore, it should be used in women of childbearing potential only when, in the judgment of the physician, the potential benefits outweigh the possible risks.

PRECAUTIONS:

Chlorzoxazone should be used with caution in patients with known allergies or with a history of allergic reactions to drugs. If a sensitivity reaction occurs such as urticaria, redness, or itching of the skin, the drug should be stopped.

If any symptoms suggestive of liver dysfunction are observed, the drug should be discontinued.

ADVERSE REACTIONS:

After extensive clinical use of chlorzoxazone-containing products, it is apparent that the drug is well-tolerated and seldom produces undesirable side effects. Occasional patients may develop gastrointestinal disturbances. It is possible in rare instances that chlorzoxazone may have been associated with gastrointestinal bleeding. Drowsiness, dizziness, lightheadedness, malaise, or overstimulation may be noted by an occasional patient. Rarely, allergic-type skin rashes, petechiae, or ecchymoses may develop during treatment. Angioneurotic edema or anaphylactic reactions are extremely rare. There is no evidence that the drug will cause renal damage. Rarely, a patient may note discoloration of the urine resulting from a phenolic metabolite of chlorzoxazone. This finding is of no known clinical significance.

OVERDOSAGE:

Symptoms:

Initially, gastrointestinal disturbances such as nausea, vomiting, or diarrhea together with drowsiness, dizziness, lightheadedness or headache may occur. Early in the course there may be malaise or sluggishness followed by marked loss of muscle tone, making voluntary movement impossible. The deep tendon reflexes may be decreased or absent. The sensorium remains intact, and there is no peripheral loss of sensation. Respiratory depression may occur with rapid, irregular respiration and intercostal and substernal retraction. The blood pressure is lowered, but shock has not been observed.

Treatment:

Gastric lavage or induction of emesis should be carried out, followed by administration of activated charcoal. Thereafter, treatment is entirely supportive. If respirations are depressed, oxygen and artificial respiration should be employed and a patent airway assured by use of an oropharyngeal airway or endotracheal tube. Hypotension may be counteracted by use of dextran, plasma, concentrated albumin or a vasopressor agent such as norepinephrine. Cholinergic drugs or analeptic drugs are of no value and should not be used.

DOSAGE AND ADMINISTRATION:

Usual Adult Dosage:

One tablet three or four times daily. If adequate response is not obtained with this dose, it may be increased to 1½ tablets (750 mg) three or four times daily. As improvement occurs dosage can usually be reduced.

HOW SUPPLIED:

Chlorzoxazone Tablets, USP are available as:

500 mg: | Light green, round, scored tablet. Debossed with 555/585 on one side and stylized barr on the other side. Available in bottles of:
 | 20 NDC 0555-0585-18
 | 100 NDC 0555-0585-02
 | 500 NDC 0555-0585-04
 | 1000 NDC 0555-0585-05

Dispense with a child-resistant closure in a tight container as defined in the USP/NF.

Store at controlled room temperature 15º-30ºC (59º-86ºF) [See USP].

MANUFACTURED BY

BARR LABORATORIES, INC.

POMONA, NY 10970

Revised SEPTEMBER 2002

BR-585

PRINCIPAL DISPLAY PANEL

NDC 55045-1594-08
Chlorzoxazone
Tablets, USP
500 mg
Rx only
100 Tablets